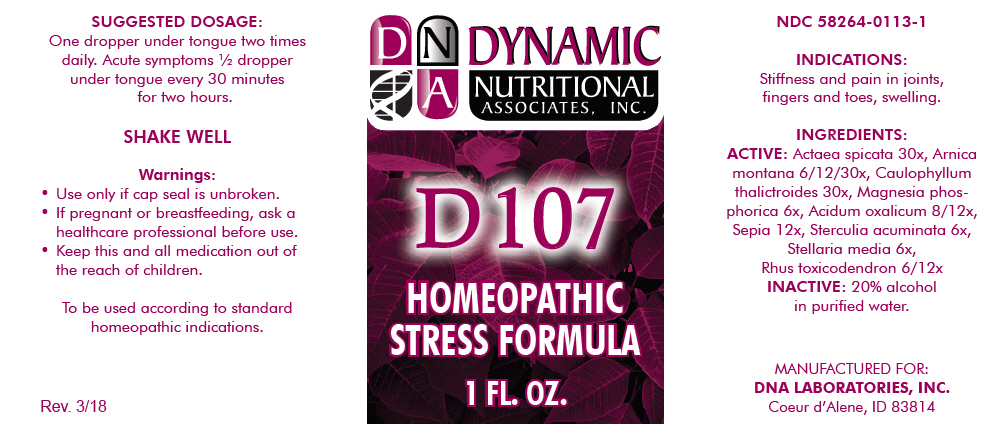 DRUG LABEL: D-107
NDC: 58264-0113 | Form: SOLUTION
Manufacturer: DNA Labs, Inc.
Category: homeopathic | Type: HUMAN OTC DRUG LABEL
Date: 20250113

ACTIVE INGREDIENTS: ACTAEA SPICATA ROOT 30 [hp_X]/1 mL; ARNICA MONTANA 6 [hp_X]/1 mL; CAULOPHYLLUM THALICTROIDES ROOT 30 [hp_X]/1 mL; MAGNESIUM PHOSPHATE, DIBASIC TRIHYDRATE 6 [hp_X]/1 mL; OXALIC ACID 8 [hp_X]/1 mL; SEPIA OFFICINALIS JUICE 12 [hp_X]/1 mL; COLA ACUMINATA SEED 6 [hp_X]/1 mL; STELLARIA MEDIA 6 [hp_X]/1 mL; TOXICODENDRON PUBESCENS LEAF 6 [hp_X]/1 mL
INACTIVE INGREDIENTS: ALCOHOL; WATER

D-107

NDC 58264-0113-1

INDICATIONS

PURPOSE

Stiffness and pain in joints, fingers and toes, swelling.

INGREDIENTS

ACTIVE

Actaea spicata 30x, Arnica montana 6/12/30x, Caulophyllum thalictroides 30x, Magnesia phosphorica 6x, Acidum oxalicum 8/12x, Sepia 12x, Sterculia acuminata 6x, Stellaria media 6x, Rhus toxicodendron 6/12x

INACTIVE

20% alcohol in purified water.

SUGGESTED DOSAGE

One dropper under tongue two times daily. Acute symptoms ½ dropper under tongue every 30 minutes for two hours.

STORAGE AND HANDLING

SHAKE WELL

Warnings

- Use only if cap seal is unbroken.

PREGNANCY OR BREAST FEEDING

- If pregnant or breastfeeding, ask a healthcare professional before use.

KEEP OUT OF REACH OF CHILDREN

- Keep this and all medication out of the reach of children.

To be used according to standard homeopathic indications.

PRINCIPAL DISPLAY PANEL - 1 FL. OZ. Bottle Label

DYNAMIC
NUTRITIONAL
ASSOCIATES, INC.

D 107

HOMEOPATHIC
STRESS FORMULA

1 FL. OZ.